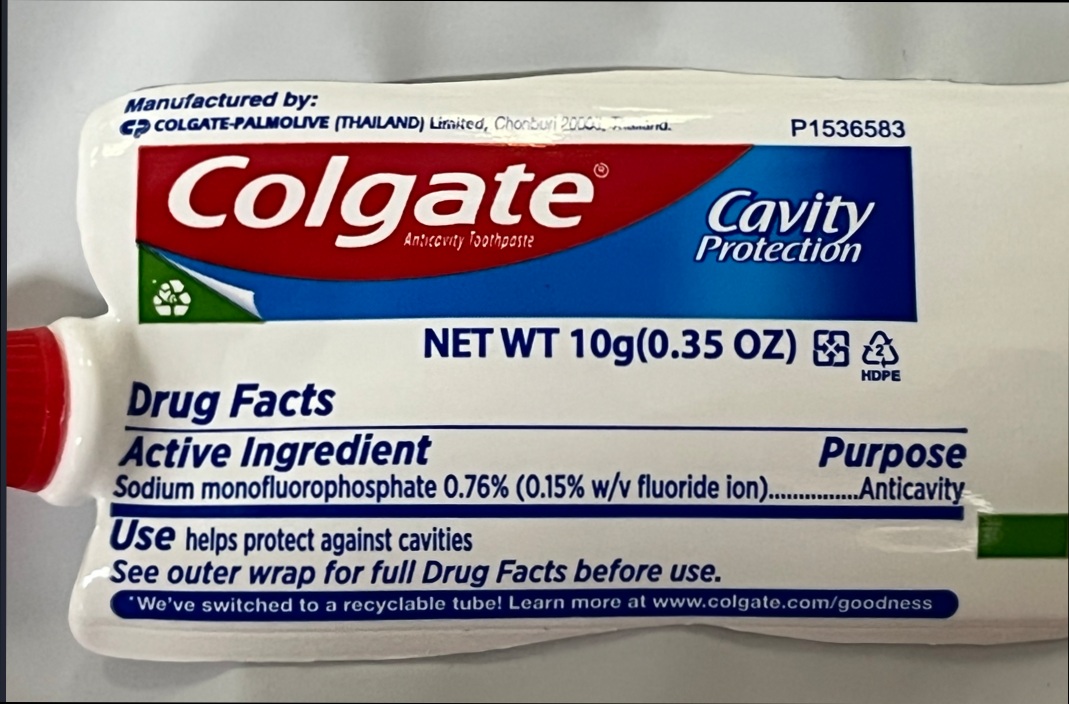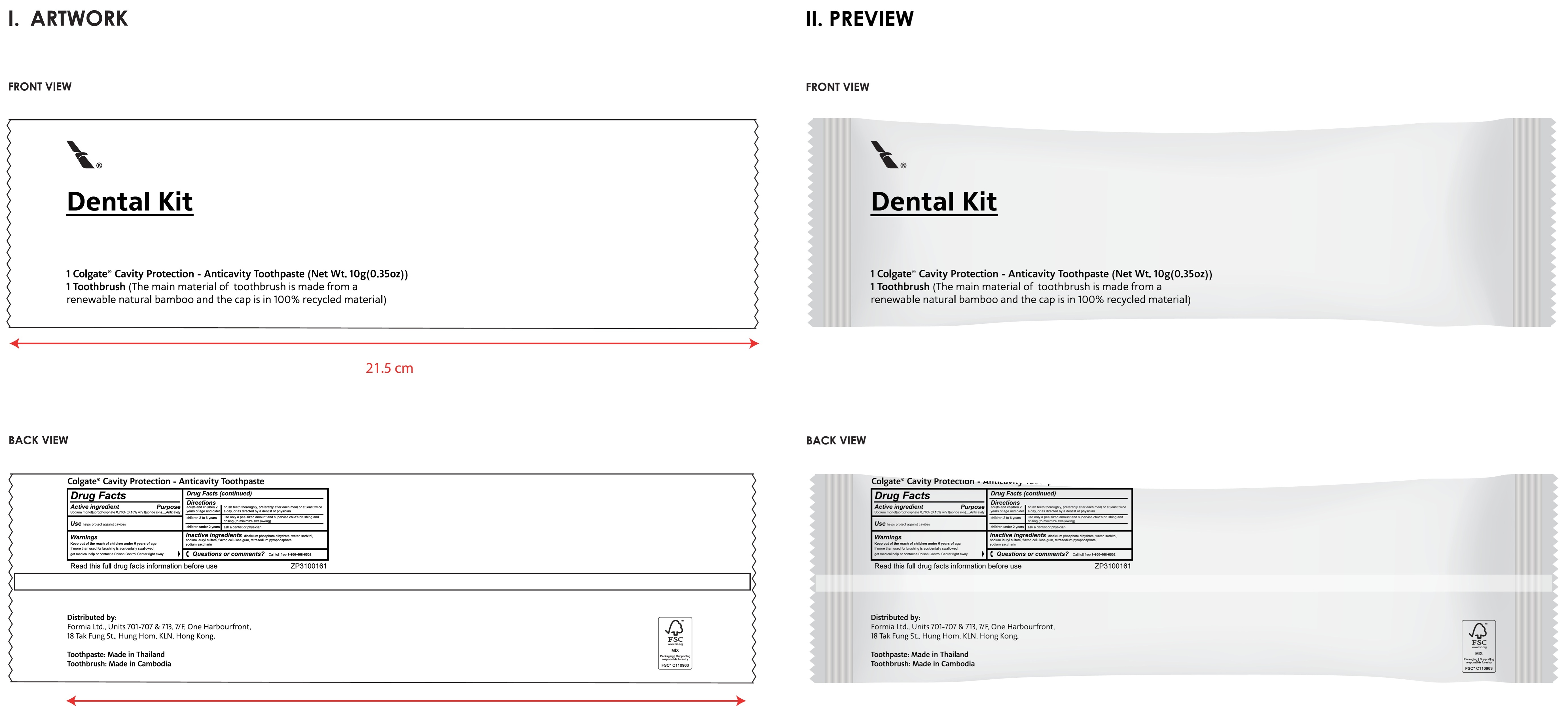 DRUG LABEL: Colgate Anticavity
NDC: 73234-040 | Form: KIT | Route: DENTAL
Manufacturer: MING FAI ENTERPRISE (CAMBODIA) CO., LTD.
Category: otc | Type: HUMAN OTC DRUG LABEL
Date: 20260225

ACTIVE INGREDIENTS: SODIUM MONOFLUOROPHOSPHATE 7.6 mg/1 g
INACTIVE INGREDIENTS: DIBASIC CALCIUM PHOSPHATE DIHYDRATE; WATER; SORBITOL; SODIUM LAURYL SULFATE; CARBOXYMETHYLCELLULOSE SODIUM, UNSPECIFIED FORM; SODIUM PYROPHOSPHATE; SACCHARIN SODIUM

Colgate Anticavity Toothpaste

Active ingredient

Sodium monofluorophosphate 0.76% (0.15% w/v fluoride ion)

Purpose

Anticavity

Use

helps protect against cavities

Warnings

Keep out of the reach of children

under 6 years of age. If more than used for brushing is accidentally swallowed, get medical help or contact a Poison Control Center right away.

Directions

adults and children 2 years of age and older | brush teeth thoroughly, preferably after each meal or at least twice a day, or as directed by a dentist or physician
children 2 to 6 years | use only a pea sized amount and supervise child's brushing and rinsing (to minimize swallowing)
children under 2 years | ask a dentist or physician

Inactive ingredients

dicalcium phosphate dihydrate, water, sorbitol, sodium lauryl sulfate, flavor, cellulose gum, tetrasodium pyrophosphate, sodium saccharin

Questions or comments?

Call toll-free 1-800-468-6502